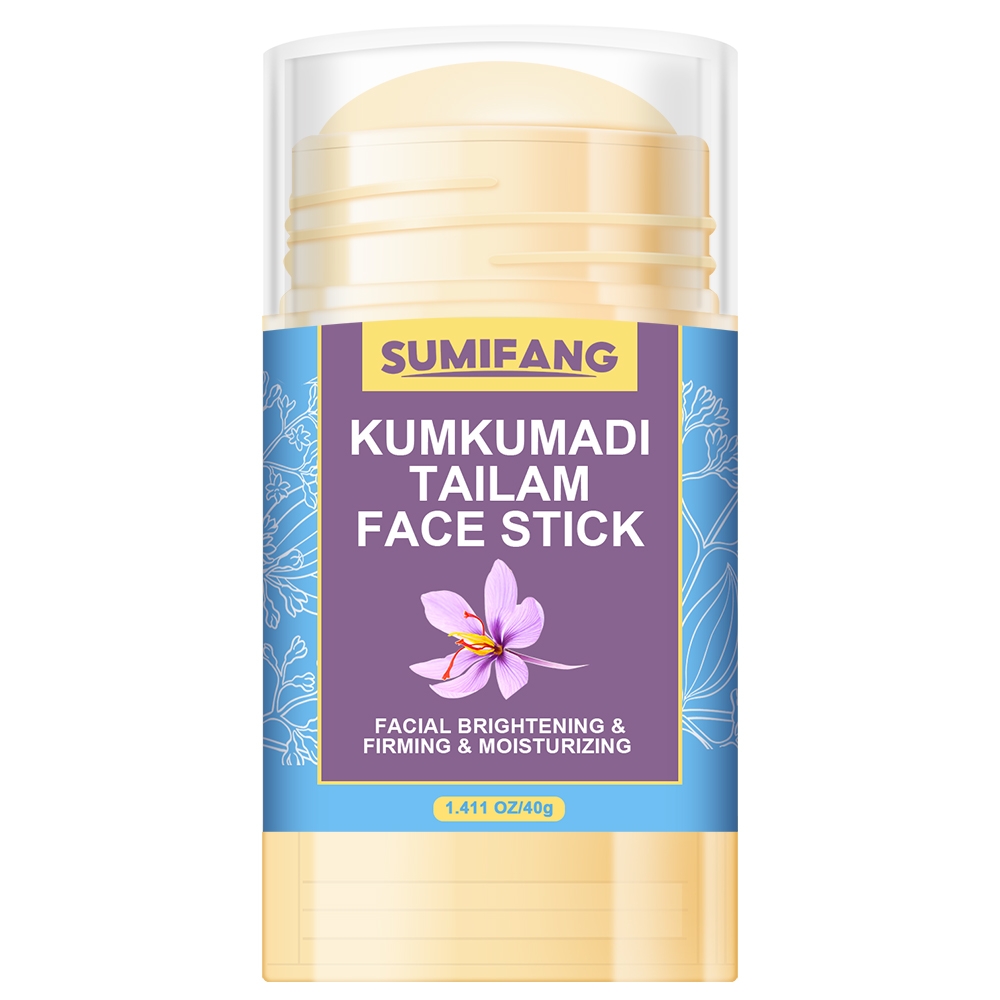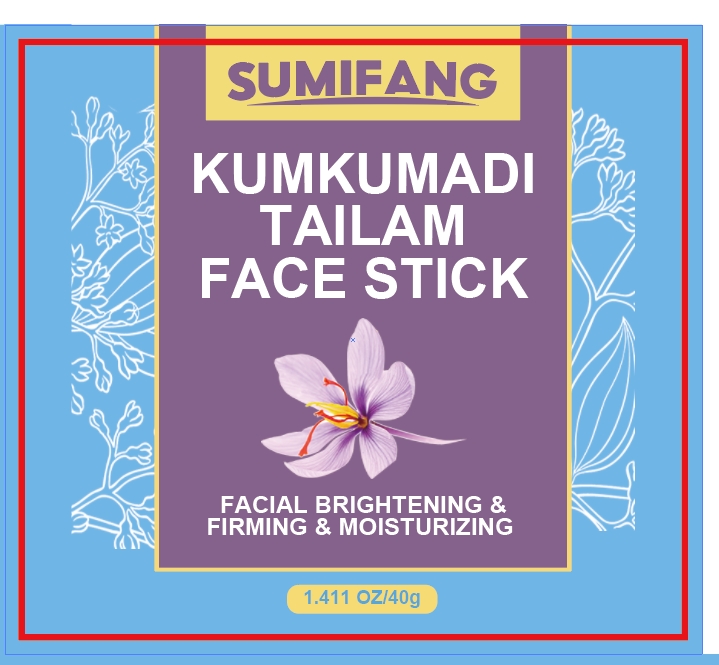 DRUG LABEL: KUMKUMADI TAILAM FACESTICK
NDC: 84025-123 | Form: STICK
Manufacturer: Guangzhou Yanxi Biotechnology Co.. Ltd
Category: otc | Type: HUMAN OTC DRUG LABEL
Date: 20240807

ACTIVE INGREDIENTS: HYDROGENATED AVOCADO OIL 5 mg/40 g
INACTIVE INGREDIENTS: WATER

DOSAGE AND ADMINISTRATION

Cream for brightening and firming facial skin

WARNINGS

Keep out of children

INACTIVE INGREDIENT

Aqua

INDICATIONS AND USAGE

For dull and dry facial skin

Keep out of children

PURPOSE

Brightens skin tone and moisturizes skin